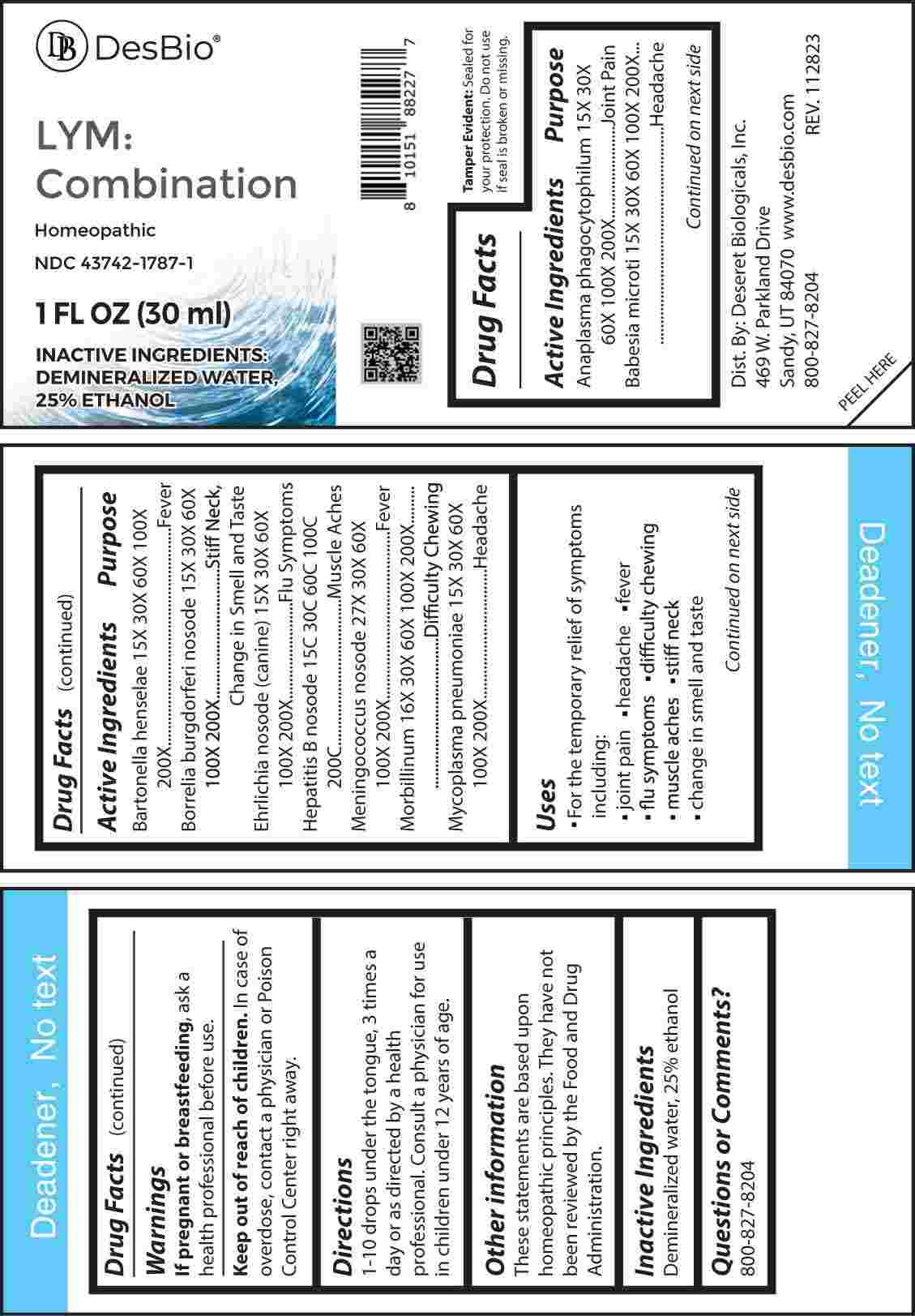 DRUG LABEL: Lym Combination
NDC: 43742-1787 | Form: LIQUID
Manufacturer: Deseret Biologicals, Inc.
Category: homeopathic | Type: HUMAN OTC DRUG LABEL
Date: 20240306

ACTIVE INGREDIENTS: ANAPLASMA PHAGOCYTOPHILUM 15 [hp_X]/1 mL; BABESIA MICROTI 15 [hp_X]/1 mL; BARTONELLA HENSELAE 15 [hp_X]/1 mL; BORRELIA BURGDORFERI 15 [hp_X]/1 mL; EHRLICHIA CANIS 15 [hp_X]/1 mL; MYCOPLASMA PNEUMONIAE 15 [hp_X]/1 mL; MEASLES VIRUS 16 [hp_X]/1 mL; NEISSERIA MENINGITIDIS 27 [hp_X]/1 mL; HEPATITIS B VIRUS 15 [hp_C]/1 mL
INACTIVE INGREDIENTS: WATER; ALCOHOL

DRUG FACTS:

ACTIVE INGREDIENTS:

Anaplasma Phagocytophilum 15X, 30X, 60X, 100X, 200X, Babesia Microti 15X, 30X, 60X, 100X, 200X, Bartonella Henselae 15X, 30X, 60X, 100X, 200X, Borrelia Burgdorferi Nosode 15X, 30X, 60X, 100X, 200X, Ehrlichia Nosode 15X, 30X, 60X, 100X, 200X, Hepatitis B Nosode 15C, 30C, 60C, 100C, 200C, Meningococcus Nosode 27X, 30X, 60X, 100X, 200X, Morbillinum 16X, 30X, 60X, 100X, 200X, Mycoplasma Pneumoniae 15X, 30X, 60X, 100X, 200X.

PURPOSE:

Anaplasma Phagocytophilum – Joint Pain, Babesia Microti - Headache, Bartonella Henselae - Fever, Borrelia Burgdorferi Nosode – Stiff Neck, Change in Smell and Taste, Ehrlichia Nosode – Flu Symptoms, Hepatitis B Nosode – Muscle Aches, Meningococcus Nosode – Fever, Morbillinum – Difficulty Chewing, Mycoplasma Pneumoniae - Headache

USES:

• For the temporarily relief of symptoms including:

• joint pain • headaches • fever

• flu symptoms • difficulty chewing

• muscle aches • stiff neck

• change in smell and taste

These statements are based upon homeopathic principles. They have not been reviewed by the Food and Drug Administration.

WARNINGS:

If pregnant or breast-feeding, ask a health professional before use.

Keep out of reach of children. In case of overdose, contact a physician or Poison Control Center right away.
Tamper Evident: Sealed for your protection. Do not use if seal is broken or missing.

KEEP OUT OF REACH OF CHILDREN:

In case of overdose, contact a physician or Poison Control Center right away.

DIRECTIONS:

1-10 drops under the tongue, 3 times a day or as directed by a health professional. Consult a physician for use in children under 12 years of age

INACTIVE INGREDIENTS:

Demineralized water, 25% ethanol

QUESTIONS:

Dist. By: Deseret Biologicals, Inc.
469 W. Parkland Drive
Sandy, UT 84070

www.desbio.com

800-827-8204

PACKAGE LABEL DISPLAY:

Des Bio

LYM: Combination

Homeopathic
NDC 43742-1787-1
1 FL OZ (30 ml)